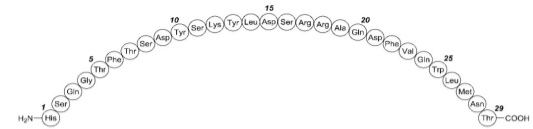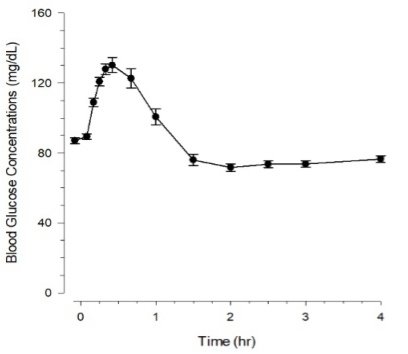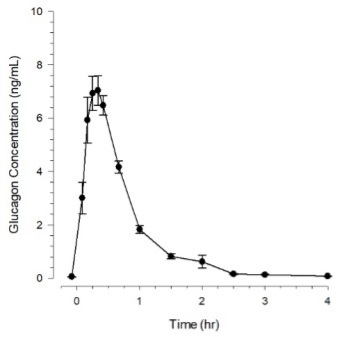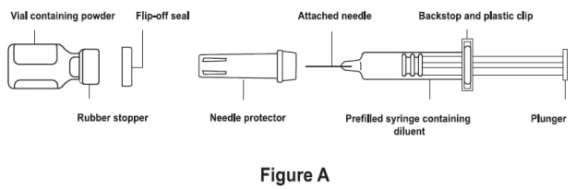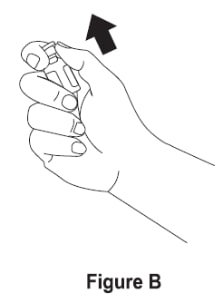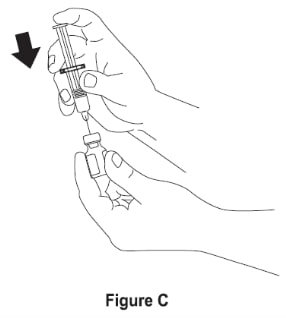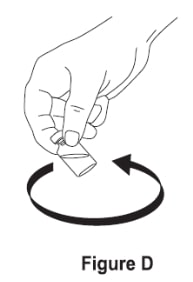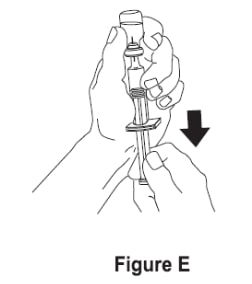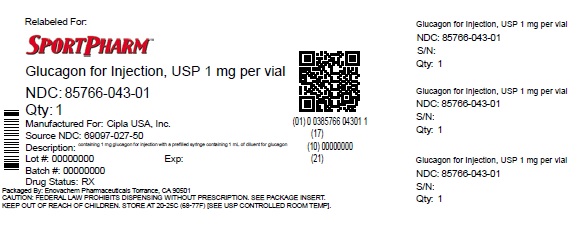 DRUG LABEL: Glucagon
NDC: 85766-043 | Form: KIT | Route: SUBCUTANEOUS
Manufacturer: Sportpharm LLC
Category: prescription | Type: HUMAN PRESCRIPTION DRUG LABEL
Date: 20260206

ACTIVE INGREDIENTS: GLUCAGON 1 mg/1 mL
INACTIVE INGREDIENTS: LACTOSE MONOHYDRATE 49 mg/1 mL; HYDROCHLORIC ACID; GLYCERIN 12 mg/1 mL; HYDROCHLORIC ACID; WATER

HIGHLIGHTS OF PRESCRIBING INFORMATION

These highlights do not include all the information needed to use GLUCAGON FOR INJECTION safely and effectively. See full prescribing information for GLUCAGON FOR INJECTION.
Glucagon for Injection, for subcutaneous, intramuscular, or intravenous use.
Initial U.S. Approval: 1960

1 INDICATIONS AND USAGE

Glucagon for injection is an antihypoglycemic agent and a gastrointestinal motility inhibitor indicated:

- for the treatment of severe hypoglycemia in pediatric and adult patients with diabetes. (1.1)
- as a diagnostic aid for use during radiologic examinations to temporarily inhibit movement of the gastrointestinal tract in adult patients. (1.2)

2 DOSAGE AND ADMINISTRATION

Dosage in adult and pediatric patients to treat severe hypoglycemia (2.2)

- Adults and Pediatric Patients Weighing 20 kg or More:
  - The recommended dosage is 1 mg (1 mL) injected subcutaneously or intramuscularly into the upper arm, thigh, or buttocks, or intravenously.
  - If there has been no response after 15 minutes, an additional 1 mg dose (1 mL) may be administered while waiting for emergency assistance.
- Pediatric Patients Weighing Less Than 20 kg:
  - The recommended dosage is 0.5 mg (0.5 mL) or dose equivalent to 20 to 30 mcg/kg injected subcutaneously or intramuscularly into the upper arm, thigh, or buttocks, or intravenously.
  - If there has been no response after 15 minutes, an additional 0.5 mg dose (0.5 mL) may be administered while waiting for emergency assistance.

Important Administration Instructions for Using Glucagon for Injection to Treat Severe Hypoglycemia (2.1)

- Glucagon for injection is for subcutaneous, intramuscular, or intravenous injection. Administer intravenously ONLY under medical supervision.
- See the Full Prescribing Information for administration instructions

Dosage in Adults for Using Glucagon for Injection as a Diagnostic Aid (2.4)

- Doses required for relaxation of the stomach, duodenum, and small bowel, depend on the onset and duration of effect required for the examination.
- The dose for relaxation of the duodenum and small bowel is 0.25 mg to 0.5 mg given intravenously or 1 mg given intramuscularly.
- For the stomach 0.5 mg intravenous or 2 mg intramuscular doses are recommended.
- For the colon, it is recommended that a 2 mg dose be administered intramuscularly approximately 10 minutes prior to the procedure.
- See the Full Prescribing Information for administration instructions (2.3)

3 DOSAGE FORMS AND STRENGTHS

For Injection: single-dose vial containing 1 mg glucagon for injection with a prefilled syringe containing 1 mL of diluent for glucagon (3)

4 CONTRAINDICATIONS

- Pheochromocytoma (4)
- Insulinoma (4)
- Known hypersensitivity to glucagon or to any of the excipients (4)
- Glucagonoma when used as a diagnostic aid (4)

5 WARNINGS AND PRECAUTIONS

- Substantial Increase in Blood Pressure in Patients with Pheochromocytoma: Contraindicated in patients with pheochromocytoma because glucagon for injection may stimulate the release of catecholamines from the tumor. (4, 5.1)
- Hypoglycemia in Patients with Insulinoma: In patients with insulinoma, glucagon administration may produce an initial increase in blood glucose; however, glucagon for injection may stimulate exaggerated insulin release from an insulinoma and cause hypoglycemia. If a patient develops symptoms of hypoglycemia after a dose of glucagon for injection, give glucose orally or intravenously. (4, 5.2)
- Hypersensitivity and Allergic Reactions: Allergic reactions, which have been reported with glucagon, may occur and include generalized rash, and in some cases anaphylactic shock with breathing difficulties, and hypotension. (4, 5.3)
- Lack of Efficacy in Patients with Decreased Glycogen:Glucagon for injection is effective in treating hypoglycemia only if sufficient hepatic glycogen is present. Patients in states of starvation, with adrenal insufficiency or chronic hypoglycemia may not have adequate levels of hepatic glycogen for glucagon for injection administration to be effective. Patients with these conditions should be treated with glucose. (5.4)
- Necrolytic Migratory Erythema (NME):Necrolytic migratory erythema (NME), a skin rash, have been reported post marketing following continuous glucagon infusion and resolved with discontinuation of the glucagon. Should NME occur, consider whether the benefits of continuous glucagon infusion outweigh the risks. (5.5)
- Hyperglycemia in Patients with Diabetes Mellitus when Used as a Diagnostic Aid: Treatment with glucagon for injection in patients with diabetes mellitus may cause hyperglycemia. Monitor diabetic patients for changes in blood glucose levels during treatment and treat if indicated. (5.6)
- Blood Pressure and Heart Rate Increase in Patients with Cardiac Disease when Used as a Diagnostic Aid: Glucagon for injection may increase myocardial oxygen demand, blood pressure, and pulse rate. Cardiac monitoring is recommended in patients with cardiac disease during use of glucagon for injection as a diagnostic aid, and an increase in blood pressure and pulse rate may require therapy. (5.7)
- Hypoglycemia in Patients with Glucagonoma:Glucagon administered to patients with glucagonoma may cause secondary hypoglycemia. Test patients suspected of having glucagonoma for blood levels of glucagon prior to treatment. (4, 5.8)

6 ADVERSE REACTIONS

Glucagon adverse reactions include: injection site reactions, nausea, vomiting, headache, dizziness, asthenia, pallor, diarrhea, somnolence, and decreased blood pressure. (6)

To report SUSPECTED ADVERSE REACTIONS, contact Cipla Ltd. at 1-866-604-3268 or FDA at 1-800-FDA-1088 or www.fda.gov/medwatch.

7 DRUG INTERACTIONS

- Beta-blockers: Patients taking beta-blockers may have a transient increase in pulse and blood pressure. (7)
- Indomethacin: In patients taking indomethacin glucagon for injection may lose its ability to raise glucose or may produce hypoglycemia. (7)
- Anticholinergic drugs: Concomitant use of anticholinergic drugs with glucagon for injection for use as a diagnostic aid is not recommended. (7)
- Warfarin: Glucagon for injection may increase the anticoagulant effect of warfarin. (7)
- Insulin: Monitor blood glucose when glucagon for injection is used as a diagnostic aid in patients receiving insulin. (7)

FULL PRESCRIBING INFORMATION

1 INDICATIONS AND USAGE

1.1 Severe Hypoglycemia

Glucagon for injection is indicated for the treatment of severe hypoglycemia in pediatric and adult patients with diabetes mellitus.

1.2 Diagnostic Aid

Glucagon for injection is indicated as a diagnostic aid for use during radiologic examinations to temporarily inhibit movement of the gastrointestinal tract in adult patients.

2 DOSAGE AND ADMINISTRATION

2.1 Important Administration Instructions for Using Glucagon for Injection to Treat Severe Hypoglycemia

Glucagon for injection is for subcutaneous, intramuscular, or intravenous injection. Administer intravenously ONLY under medical supervision.

Instruct patients and their caregivers on the signs and symptoms of severe hypoglycemia. Because severe hypoglycemia requires the help of others to recover, instruct the patient to inform those around them about glucagon for injection and its Instructions for Use. Administer glucagon for injection as soon as possible when severe hypoglycemia is recognized.

Instruct the patient or caregiver to read the Instructions for Use at the time they receive a prescription for glucagon for injection. Emphasize the following instructions to the patient or caregiver:

- Using the supplied prefilled syringe, carefully insert the needle through the rubber stopper of the vial containing glucagon for injection powder and inject all the liquid from the syringe into the vial.
- Swirl the vial gently until the powder is completely dissolved and no particles remain in the fluid. The reconstituted solution should be clear and of a water-like consistency at time of use. Inspect visually for particulate matter and discoloration. If the resulting solution is cloudy or contains particulate matter do not use.
- The reconstituted solution is 1 mg per mL glucagon. Use immediately after reconstitution.
- Immediately after reconstitution, use the same syringe to withdraw the correct dose of glucagon for injection.
- Inject the solution subcutaneously or intramuscularly in the upper arm, thigh, or buttocks. In addition, healthcare providers may administer intravenously.
- Call for emergency assistance immediately after administering the dose.
- If there has been no response after 15 minutes, an additional dose of glucagon for injection may be administered while waiting for emergency assistance.
- When the patient has responded to the treatment and is able to swallow, give oral carbohydrates to restore the liver glycogen and prevent recurrence of hypoglycemia.
- Discard any unused portion.

2.2 Dosage for Treatment of Severe Hypoglycemia

Adults and Pediatric Patients Weighing 20 kg or More

- The recommended dosage is 1 mg (1 mL) injected subcutaneously or intramuscularly into the upper arm, thigh, or buttocks. Alternatively, healthcare providers may administer the dose intravenously.
- If there has been no response after 15 minutes, an additional 1 mg dose (1 mL) of glucagon for injection may be administered while waiting for emergency assistance.

Pediatric Patients Weighing Less Than 20 kg

- The recommended dosage is 0.5 mg (0.5 mL) or dose equivalent to 20 to 30 mcg/kg injected subcutaneously or intramuscularly into the upper arm, thigh, or buttocks. Alternatively, healthcare providers may administer the dose intravenously.
- If there has been no response after 15 minutes, an additional 0.5 mg dose (0.5 mL) of glucagon for injection may be administered while waiting for emergency assistance.

2.3 Important Administration Instructions for Using Glucagon for Injection as a Diagnostic Aid

- Reconstitute glucagon for injection with 1 mL of diluent.
- Swirl the vial gently until the powder is completely dissolved and no particles remain in the fluid. The reconstituted solution should be clear and of a water-like consistency at time of use. Inspect visually for particulate matter and discoloration. If the resulting solution is cloudy or contains particulate matter do not use.
- Withdraw the correct dose of glucagon for injection.
- The reconstituted solution is 1 mg per mL glucagon.
- Immediately after reconstitution, inject the solution intravenously or intramuscularly into upper arm, thigh, or buttocks.
- Discard unused portion.
- After the end of the diagnostic procedure, give oral carbohydrates to patients who have been fasting, if this is compatible with the diagnostic procedure.

2.4 Dosage in Adults for Use as a Diagnostic Aid

- Doses required for relaxation of the stomach, duodenum, and small bowel, depend on the onset and duration of effect required for the examination [see Pharmacodynamics (12.2)].
- The usual dose for relaxation of the stomach, duodenum and small bowel is 0.25 mg to 0.5 mg given intravenously or 1 mg given intramuscularly, but up to 2 mg intravenously or intramuscularly may be used if required (2 mg doses produce a higher rate of nausea and vomiting than lower doses) [see Adverse Reactions (6)].
- For the stomach because it is less sensitive to the effect of glucagon, 0.5 mg intravenous or 2 mg intramuscular doses are recommended.
- For the examination of the colon, it is recommended that a 2 mg dose be administered intramuscularly approximately 10 minutes prior to the procedure.

3 DOSAGE FORMS AND STRENGTHS

Glucagon for injection, USP is a white to off white lyophilized powder supplied as follows:

- Single-dose vial containing 1 mg glucagon for injection with a pre-filled syringe containing 1 mL of diluent for glucagon.

4 CONTRAINDICATIONS

Glucagon for injection is contraindicated in patients with:

- Pheochromocytoma because of the risk of substantial increase in blood pressure [see Warnings and Precautions (5.1)]
- Insulinoma because of the risk of hypoglycemia [see Warnings and Precautions (5.2)]
- Known hypersensitivity to glucagon or any of the excipients in glucagon for injection. Allergic reactions have been reported with glucagon and include anaphylactic shock with breathing difficulties and hypotension [see Warnings and Precautions (5.3)]
- Glucagonoma when used as a diagnostic aid because of the risk of hypoglycemia [see Warnings and Precautions (5.8)]

5 WARNINGS AND PRECAUTIONS

5.1 Substantial Increase in Blood Pressure in Patients with Pheochromocytoma

Glucagon for injection is contraindicated in patients with pheochromocytoma because glucagon may stimulate the release of catecholamines from the tumor [see Contraindications (4)]. If the patient develops a substantial increase in blood pressure and a previously undiagnosed pheochromocytoma is suspected, 5 to 10 mg of phentolamine mesylate, administered intravenously, has been shown to be effective in lowering blood pressure.

5.2 Hypoglycemia in Patients with Insulinoma

In patients with insulinoma, administration of glucagon may produce an initial increase in blood glucose; however, glucagon for injection administration may directly or indirectly (through an initial rise in blood glucose) stimulate exaggerated insulin release from an insulinoma and cause hypoglycemia. Glucagon for injection is contraindicated in patients with insulinoma [see Contraindications (4)]. If a patient develops symptoms of hypoglycemia after a dose of glucagon for injection, give glucose orally or intravenously.

5.3 Hypersensitivity and Allergic Reactions

Allergic reactions have been reported with glucagon, these include generalized rash, and in some cases anaphylactic shock with breathing difficulties and hypotension. Glucagon for injection is contraindicated in patients with a prior hypersensitivity reaction [see Contraindications (4)].

5.4 Lack of Efficacy in Patients with Decreased Hepatic Glycogen

Glucagon for injection is effective in treating hypoglycemia only if sufficient hepatic glycogen is present. Patients in states of starvation, with adrenal insufficiency or chronic hypoglycemia may not have adequate levels of hepatic glycogen for glucagon for injection administration to be effective. Patients with these conditions should be treated with glucose.

5.5 Necrolytic Migratory Erythema

Necrolytic Migratory Erythema (NME), a skin rash commonly associated with glucagonomas (glucagon-producing tumors) and characterized by scaly, pruritic erythematous plaques, bullae, and erosions, has been reported post marketing following continuous glucagon infusion. NME lesions may affect the face, groin, perineum and legs or be more widespread. In the reported cases, NME resolved with discontinuation of the glucagon, and treatment with corticosteroids was not effective. Should NME occur, consider whether the benefits of continuous glucagon infusion outweigh the risks.

5.6 Hyperglycemia in Patients with Diabetes Mellitus when Used as a Diagnostic Aid

Treatment with glucagon for injection in patients with diabetes mellitus may cause hyperglycemia. Monitor diabetic patients for changes in blood glucose levels during treatment and treat if indicated.

5.7 Blood Pressure and Heart Rate Increase in Patients with Cardiac Disease when Used as a Diagnostic Aid

Glucagon for injection may increase myocardial oxygen demand, blood pressure, and pulse rate which may be life-threatening in patients with cardiac disease. Cardiac monitoring is recommended in patients with cardiac disease during use of glucagon for injection as a diagnostic aid, and an increase in blood pressure and pulse rate may require therapy.

5.8 Hypoglycemia in Patients with Glucagonoma

Glucagon administered to patients with glucagonoma may cause secondary hypoglycemia. Test patients suspected of having glucagonoma for blood levels of glucagon prior to use as a diagnostic aid as glucagon for injection is contraindicated in this setting [see Contraindications (4)].

6 ADVERSE REACTIONS

The following important adverse reactions are described below and elsewhere in the labeling:

- Hypersensitivity and Allergic Reactions [see Warnings and Precautions (5.3)]
- Necrolytic Migratory Erythema [see Warnings and Precautions (5.5)]
- Hyperglycemia in Patients with Diabetes Mellitus when Used as a Diagnostic Aid [see Warnings and Precautions (5.6)]
- Blood Pressure and Heart Rate Increase in Patients with Cardiac Disease when used as a Diagnostic Aid [see Warnings and Precautions (5.7)]

The following adverse reactions have been identified during post-approval use of glucagon. Because these reactions are reported voluntarily from a population of uncertain size, it is generally not possible to reliably estimate their frequency or establish a causal relationship to drug exposure.

- Injection site reactions including erythema and swelling
- Nausea
- Vomiting
- Headache
- Dizziness
- Asthenia
- Pallor
- Diarrhea
- Somnolence
- Generalized allergic reactions including anaphylactic shock with breathing difficulties and hypotension
- Hypertension and tachycardia
- Decreased blood pressure. Hypotension has been reported up to 2 hours after administration in patients receiving glucagon as premedication for upper gastrointestinal endoscopy procedures.
- Hypoglycemia and hypoglycemic coma. Patients taking indomethacin may be more likely to experience hypoglycemia following glucagon administration [see Drug Interactions (7)].
- Necrolytic Migratory Erythema (NME) cases have been reported post marketing in patients receiving continuous infusion of glucagon.

7 DRUG INTERACTIONS

Table 1: Clinically Significant Drug Interactions with Glucagon for Injection

Beta-Blockers
Clinical Impact: | Patients taking beta-blockers may have a transient increase in pulse and blood pressure when given glucagon for injection.
Intervention: | The increase in blood pressure and heart rate may require therapy in patients with coronary artery disease.
Indomethacin
Clinical Impact: | In patients taking indomethacin, glucagon for injection may lose its ability to raise blood glucose or may even produce hypoglycemia.
Intervention: | Monitor blood glucose levels during glucagon treatment of patients taking indomethacin.
Anticholinergic Drugs
Clinical Impact: | The concomitant use of anticholinergic drugs and glucagon for injection increase the risk of gastrointestinal adverse reactions due to additive effects on inhibition of gastrointestinal motility.
Intervention: | Concomitant use of anticholinergic drugs with glucagon for injection for use as a diagnostic aid is not recommended.
Warfarin
Clinical Impact: | Glucagon for injection may increase the anticoagulant effect of warfarin.
Intervention: | Monitor patients for unusual bruising or bleeding, as adjustments in warfarin dosage may be required.
Insulin
Clinical Impact: | Insulin acts antagonistically to glucagon.
Intervention: | Monitor blood glucose when glucagon for injection is used as a diagnostic aid in patients receiving insulin.

8 USE IN SPECIFIC POPULATIONS

8.1 Pregnancy

Risk Summary

Available data from case reports and a small number of observational studies with glucagon use in pregnant women over decades of use have not identified a drug-associated risk of major birth defects, miscarriage or adverse maternal or fetal outcomes. Multiple small studies have demonstrated a lack of transfer of pancreatic glucagon across the human placental barrier during early gestation. In a rat reproduction study, no embryofetal toxicity was observed with glucagon administered by injection during the period of organogenesis at doses representing up to 40 times the human dose, based on body surface area (mg/m^2) (see Data).

The estimated background risk of major birth defects and miscarriage for the indicated population is unknown. In the U.S. general population, the estimated background risk of major birth defects and miscarriage in clinically recognized pregnancies is 2%-4% and 15%-20%, respectively.

Data

Animal Data

In pregnant rats given animal sourced glucagon twice-daily by injection at doses up to 2 mg/kg (up to 40 times the human dose based on body surface area extrapolation, mg/m^2) during the period of organogenesis, there was no evidence of increased malformations or embryofetal lethality.

8.2 Lactation

Risk Summary

There is no information available on the presence of glucagon in human or animal milk, the effects of glucagon on the breastfed child or the effects of glucagon on milk production. However, glucagon is a peptide and would be expected to be broken down to its constituent amino acids in the infant's digestive tract and is therefore, unlikely to cause harm to an exposed infant.

8.4 Pediatric Use

The safety and effectiveness of glucagon for injection for the treatment of severe hypoglycemia in pediatric patients with diabetes have been established.

Safety and effectiveness for use as a diagnostic aid during radiologic examinations to temporarily inhibit movement of the gastrointestinal tract in pediatric patients have not been established.

8.5 Geriatric Use

Clinical studies of glucagon did not include sufficient numbers of subjects aged 65 and over to determine whether they respond differently from younger subjects. Other reported clinical experience has not identified differences in responses between the elderly and younger patients. In general, dose selection for an elderly patient when used as a diagnostic aid should be cautious, usually starting at the low end of the dosing range, reflecting the greater frequency of decreased hepatic, renal, or cardiac function, and of concomitant disease or other drug therapy.

10 OVERDOSAGE

If overdosage occurs, the patient may experience nausea, vomiting, inhibition of GI tract motility, increase in blood pressure and pulse rate. In case of suspected overdosing, the serum potassium may decrease and should be monitored and corrected if needed. If the patient develops a dramatic increase in blood pressure, phentolamine mesylate has been shown to be effective in lowering blood pressure for the short time that control would be needed.

11 DESCRIPTION

Glucagon is an antihypoglycemic agent and a gastrointestinal motility inhibitor. Glucagon is synthesized by solid phase peptide synthesis. The chemical structure of the glucagon is identical to human glucagon. Glucagon is a single-chain polypeptide that contains 29 amino acid residues and has a molecular weight of 3483 Daltons.

The empirical formula is C153H225N43O49S. The primary sequence of glucagon is shown below.

Crystalline glucagon is a white to off-white powder. It is relatively insoluble in water but is soluble at a pH of less than 3 or more than 9.5.

Glucagon for injection, USP is a sterile lyophilized white to off white powder in a vial and a syringe of sterile diluent for intravenous, intramuscular, or subcutaneous use. The vial contains 1 mg of glucagon, 49 mg of lactose monohydrate. Hydrochloric acid may have been added during manufacture to adjust the pH of the glucagon to 2.5 to 3.0. One International Unit of glucagon is equivalent to 1 mg of glucagon. The 1-mL diluent syringe contains 12 mg of glycerin, 1 mg hydrochloric acid, and Water for Injection, at pH 1.8 to 2.2.

12 CLINICAL PHARMACOLOGY

12.1 Mechanism of Action

Glucagon increases blood glucose concentration by activating hepatic glucagon receptors, thereby stimulating glycogen breakdown and release of glucose from the liver. Hepatic stores of glycogen are necessary for glucagon to produce an antihypoglycemic effect. Extrahepatic effects of glucagon include relaxation of the smooth muscle of the stomach, duodenum, small bowel, and colon.

12.2 Pharmacodynamics

Treatment of Severe Hypoglycemia

Blood glucose concentrations rise within 10 minutes of subcutaneous injection and mean maximal concentration of 136 mg/dL is attained 30 minutes after injection (see Figure 1). Similarly, following intramuscular injection, the mean peak glucose level was 138 mg/dL, which occurred at 26 minutes after injection.

Figure 1 Mean (SE) blood glucose concentrations after subcutaneous injection of glucagon (1 mg) in 25 normal volunteers

Diagnostic Aid

Table 2 displays the dose and pharmacodynamics properties of glucagon for injection as a diagnostic aid during radiological examination.

Table 2: Dose and Pharmacodynamic properties of Glucagon for Injection as a Diagnostic Aid

Dose | Route of administration | Time of onset of action | Approximate duration of effect
0.25 – 0.5 mg | Intravenous | 1 minute | 9 – 17 minutes
1 mg | Intramuscular | 8 – 10 minutes | 12 – 27 minutes
2 mg* | Intravenous | 1 minute | 22 – 25 minutes
2 mg* | Intramuscular | 4 – 7 minutes | 21 – 32 minutes

* Administration of 2 mg doses produces a higher incidence of nausea and vomiting than do lower doses.

12.3 Pharmacokinetics

Absorption

Glucagon injected through the intramuscular route achieved mean peak plasma levels of 6.9 ng/mL at approximately 13 minutes after dosing; and 7.9 ng/mL at approximately 20 minutes after subcutaneous dosing. Administration of the intravenous glucagon showed dose proportionality of the pharmacokinetics between 0.25 and 2 mg.

Figure 2 Mean (SE) serum glucagon concentrations after subcutaneous injection of glucagon (1 mg) in 25 normal volunteers

Distribution

The mean volume of distribution was 0.25 L/kg.

Elimination

The mean clearance was 13.5 mL/min/kg. The mean half-life ranged from 8 to 18 minutes.

Metabolism

Glucagon is degraded in the liver, kidney and plasma.

13 NONCLINICAL TOXICOLOGY

13.1 Carcinogenesis, Mutagenesis, Impairment of Fertility

Long term studies in animals to evaluate carcinogenic potential have not been performed. Recombinant glucagon was positive in the bacterial Ames assay. It was determined that an increase in colony counts was related to technical difficulties in running this assay with peptides. Studies in rats have shown that glucagon does not cause impaired fertility.

16 HOW SUPPLIED/STORAGE AND HANDLING

16.1 How Supplied

Glucagon Emergency Kit for Low Blood Sugar contains 1 mg glucagon for injection, USP (a lyophilized white to off-white powder) in a single-dose vial and 1 prefilled syringe containing 1 mL of diluent of glucagon.

- NDC 85766-043-01 (relabeled from NDC 69097-027-50)

16.2 Storage and Handling

Before Reconstitution:

Store glucagon for injection at 68°F to 77°F (20°C to 25°C). Do not use glucagon for injection if the expiration date has passed. Do not freeze. Keep in its original package and away from light.

After Reconstitution:

Use reconstituted glucagon for injection immediately. Discard unused portion [see Dosage and Administration (2.3)].

17 PATIENT COUNSELING INFORMATION

Advise the patient to read the FDA-approved patient labeling (Patient Information and Instructions for Use).

Recognition of Severe Hypoglycemia

Inform patient and family members or caregivers on how to recognize the signs and symptoms of severe hypoglycemia and the risks of prolonged hypoglycemia.

Administration

Review the Patient Information and Instructions for Use with the patient and family members or caregivers.

Serious Hypersensitivity

Inform patients that allergic reactions can occur with glucagon for injection. Advise patients to seek immediate medical attention if they experience any symptoms of serious hypersensitivity reactions [see Warnings and Precautions (5.3)].

Distributed by:

Sportpharm LLC

379 Van Ness Ave 1401,

Torrance, CA 90501

Relabeled by:

Enovachem PHARMACEUTICALS

Torrance, CA 90501

PATIENT MEDICATION INFORMATION SECTION

PATIENT INFORMATION Glucagon (GLOO-ka-gon) for Injectionfor subcutaneous, intramuscular, or intravenous use

What is Glucagon for Injection?

Glucagon for Injection is a prescription medicine used:

- to treat very low blood sugar (severe hypoglycemia) in people with diabetes mellitus.
- to stop movement in the intestines in people receiving radiology exams.

Who should not use Glucagon for Injection?

Do notuse Glucagon for Injection if:

- you have a tumor in the gland on top of your kidneys (adrenal gland) called a pheochromocytoma.
- you have a tumor in your pancreas called an insulinoma.
- you have a tumor in your pancreas called a glucagonoma because it could cause low blood sugar when used for your radiology exam
- you are allergic to glucagon or lactose or any of the ingredients in Glucagon for Injection. See the end of this Patient Information leaflet for a complete list of ingredients in Glucagon for Injection.

Before using Glucagon for Injection, tell your healthcare provider about all of your medical conditions, including if you:

- have adrenal problems.
- have pancreas problems.
- have not had anything to eat or have not had a drink of water for a long time (prolonged fasting or starvation).
- have low blood sugar that does not go away (chronic hypoglycemia).
- have heart problems.
- are pregnant or plan to become pregnant. It is not known if glucagon will harm your unborn baby.
- are breastfeeding or plan to breastfeed. It is not known if glucagon passes into your breast milk.

Tell your healthcare provider about all the medicines you take, including prescription and over-the-counter medicines, vitamins and herbal supplements. Glucagon may affect the way other medicines work, and other medicines may affect how glucagon works. Know the medicines you take. Keep a list of them to show your healthcare provider and pharmacist when you get a new medicine.

How should I use Glucagon for Injection?

- Read the detailed Instructions for Usethat come with Glucagon for Injection.
- Use Glucagon for Injection exactly how and when your healthcare provider tells you to use it.
- Make sure you and your caregiver knows where you keep your Glucagon for Injection and how to use Glucagon for Injection the right way beforeyou need their help.
- Act quickly. Having very low blood sugar for a period of time may be harmful.
- After glucagon is mixed, make sure it is clear and of water-like consistency. Do not use if it has particles or is discolored.
- After giving Glucagon for Injection the caregiver should call for emergency medical help right away.
- Turn the person on their side to prevent them from choking.
- If the person does not respond after 15 minutes, another dose may be given, if available while waiting for emergency medical help.
- Eat sugar or a sugar sweetened product such as a regular soft drink or fruit juice as soon as you are able to swallow.

Tell your healthcare provider each time you use Glucagon for Injection. Your healthcare provider may need to change the dose of your diabetes medicines.

What are the possible side effects of Glucagon for Injection?

Glucagon may cause serious side effects, including:

- High blood pressure.Glucagon can cause high blood pressure in certain people with tumors in their adrenal glands called pheochromocytoma.
- Low blood sugar.Glucagon can cause low blood sugar in people with tumors in their pancreas called insulinomas and glucagonomas. Signs and symptoms of low blood sugar may include:

- sweating
- drowsiness
- dizziness
- sleep disturbances
- irregular heartbeat
- anxiety
- tremor

- blurred vision
- hunger
- slurred speech
- restlessness
- depressed mood
- tingling in the hands, feet, lips or tongue
- irritability

- abnormal behavior
- lightheadedness
- unsteady movement
- inability to concentrate
- personality changes
- headache

Very low blood sugar can cause confusion, seizures, passing out (loss of consciousness) and death. Talk to your healthcare provider about how to tell if you have low blood sugar and what to do if this happens while using Glucagon for Injection. Know your symptoms of low blood sugar. Follow your healthcare provider’s instructions for treat low blood sugar.

- Serious allergic reactions.Call your healthcare provider or get medical help right awayif you have a serious allergic reaction including:

- rash
- difficulty breathing

- low blood pressure

- High blood sugar.If you receive Glucagon for Injection before your radiology exam, it can cause high blood sugar. Your healthcare provider will monitor your blood sugar levels during your treatment.
- Heart problems.If you have heart problems and receive Glucagon for Injection before your radiology exam, you may have an increase in your blood pressure and pulse while using Glucagon for Injection which could be life threatening. Your healthcare providerwill monitor your heart during treatment.

The most common side effects of Glucagon for Injection include:

- swelling at the injection site
- redness at the injection site
- vomiting
- nausea
- decreased blood pressure
- weakness

- headache
- dizziness
- pale skin
- diarrhea
- sleepiness or drowsiness

Tell your healthcare provider if you have any side effect that bothers you or that does not go away. These are not all the possible side effects of Glucagon for Injection. For more information, ask your healthcare provider.

Call your doctor for medical advice about side effects. You may report side effects to FDA at 1-800-FDA-1088.

How should I store Glucagon for Injection?

Before you mix the Glucagon powder and liquid:

- Do not use Glucagon for Injection if the expiration date has passed.
- Store Glucagon for Injection at room temperature between 68°F to 77°F (20°C to 25°C).
- Do not freeze Glucagon for Injection.
- Keep Glucagon for Injection in its original package and away from light.

After you mix the glucagon powder and liquid:

- Use Glucagon for Injection right away.
- Throw away unused Glucagon for Injection.

Keep Glucagon for Injection and all medicines out of the reach of children.

General Information about the safe and effective use of Glucagon for Injection.

Medicines are sometimes prescribed for purposes other than those listed in a Patient Information leaflet. Do not use Glucagon for Injection for a condition for which it was not prescribed. Do not give Glucagon for Injection to other people, even if they have the same symptoms that you have. It may harm them. You can ask your pharmacist or healthcare provider for information about Glucagon for Injection that is written for health professionals.

What are the ingredients in the Glucagon for Injection?

Active Ingredient:Glucagon

Inactive ingredients:lactose monohydrate, hydrochloric acid, and water for injection

Distributed by:

Sportpharm LLC

379 Van Ness Ave 1401,

Torrance, CA 90501

Relabeled by:

Enovachem PHARMACEUTICALS

Torrance, CA 90501

This Patient Information has been approved by the U.S. Food and Drug Administration

Issued:2/2023

INSTRUCTIONS FOR USE SECTION

INSTRUCTIONS FOR USE Glucagon (GLOO-ka-gon) for injection

Important

- Read and become familiar with this Instructions for Use before an emergency happens.
- Show your family members and others where you keep your Glucagon Emergency Kit for Low Blood Sugar and how to use it the right way.
- Call for emergency medical help right after you use Glucagon for Injection.
- Do not share your Glucagon syringes or needles with another person. You may give other people a serious infection or get a serious infection from them.
- The prefilled syringe that comes with your Glucagon Emergency Kit for Low Blood Sugar is for use with Glucagon for Injection only. Do not use Glucagon for Injection syringes to inject other medicines.

How should I store Glucagon forI njection?

Before you mix the glucagon powder and liquid:

- Store Glucagon for Injection at room temperature between 68° to 77°F (20° to 25°C).
- Check the expiration date on the vial of Glucagon for Injection. Do not use Glucagon for Injection if the expiration date has passed.
- Do not freeze Glucagon for Injection.
- Keep Glucagon for Injection in its original package and away from light.

After you mix the glucagon powder and liquid:

- Use Glucagon for Injection right away.
- Throw away unused Glucagon for Injection.

Supplies you will need for your Glucagon forI njection

- Glucagon Emergency Kit for Low Blood Sugar contains (see Figure A):
- 1 single-dose vial containing 1 mg Glucagon for Injection (as a sterile, lyophilized white to off-white powder)
- 1 prefilled syringe containing 1 mL of diluent for glucagon

- 1 puncture resistant container for throwing away used needles and syringes. See “How should I dispose of (throw away) used Glucagon syringes?” at the end of these instructions.
- Alcohol swab (not included in kit)

Preparing to Inject Glucagon for Injection

- The Glucagon medicine comes as a dry powder. Before you use Glucagon for Injection, you must mix the dry powder with the syringe of diluent that comes in the Glucagon Emergency Kit for Low Blood Sugar. Do not use any other liquid to mix the medicine.

Step 1:Remove the flip-off seal from the vial of Glucagon. Wipe the rubber stopper on the vial with an alcohol swab (see Figure B).

Step 2:Remove the needle protector from the syringe. Inject all of the diluent in the prefilled syringe into the vial containing Glucagon powder (see Figure C). Do notremove the plastic clip from the syringe. Remove syringe from the vial.

Step 3:Swirl the vial gently until the Glucagon powder dissolves completely (see Figure D). Glucagon should notbe used unless the solution is clear and of a water-like consistency.

Step 4:Using the same syringe, hold the vial upside down and, making sure the needle tip remains in the solution, gently withdraw all the solution (1 mg mark on syringe) from the vial (see Figure E). The backstop and plastic clip on the syringe will prevent the rubber stopper from being pulled out of the syringe; however, if the plunger rod separates from the rubber stopper, simply reinsert the rod by turning it clockwise. The usual adult dose is 1 mg. For children weighing less than 44 lb (20 kg), give 1/2 adult dose (0.5 mg). For these children, withdraw 1/2 of the solution from the vial (0.5 mg mark on syringe).

Injecting Glucagon for Injection

Step 5:Choose your injection site and clean with an alcohol wipe. Injection sites for Glucagon for Injection are the buttocks, upper arm, or thigh.

Step 6:Insert the needle into the loose tissue under the clean injection site and push the plunger to inject all (or 1/2 for children weighing less than 44 lbs.) of the Glucagon for Injection.

After injecting Glucagon for Injection

Step 7:Apply light pressure at the injection site and withdraw the needle. Press an alcohol swab against the injection site.

Throw away your used syringe with the needle attached and any Glucagon that you did not use in an FDA-cleared sharps disposal container right away after use.

See “How should I dispose of (throw away) used Glucagon syringes?” at the end of these instructions.

Step 8:Turn the person on their side. When an unconscious person wakes up, they may vomit. Turning the person on their side will prevent them from choking.

Step 9:Call for emergency medical help right away.

Step 10:Feed the person as soon as they wake up and are able to swallow. Give the person a fast-acting source of sugar (such as a regular soft drink or fruit juice) and a long-acting source of sugar (such as crackers and cheese or a meat sandwich).

Step 11:If the person does not awaken within 15 minutes, give another dose of Glucagon and inform a doctor or emergency services right away.

Step 12:Even if the Glucagon revives the person, their doctor should be notified right away. A doctor should be notified whenever severe hypoglycemia occurs.

Hypoglycemia may happen again after receiving Glucagon for Injection.

Early symptoms of hypoglycemia (low blood glucose) include:

- sweating
- drowsiness
- dizziness
- sleep disturbances
- irregular heartbeat
- anxiety
- tremor
- blurred vision
- hunger
- slurred speech
- restlessness

- depressed mood
- tingling in the hands, feet, lips or tongue.
- irritability
- abnormal behavior
- lightheadedness
- unsteady movement
- inability to concentrate
- personality change
- headache

If not treated early, the symptoms may progress to severe hypoglycemia. Signs include:

- confusion
- unconsciousness

- seizures
- death

How should I dispose of (throw away) used Glucagon syringes?

- Put used syringes in an FDA-cleared sharps disposal container right away after use. Do not throw away (dispose of) loose needles and syringes in your household trash.
- If you do not have an FDA-cleared sharps disposal container, you may use a household container that is:
- made of a heavy-duty plastic,
- can be closed with a tight-fitting, puncture-resistant lid, without sharps being able to come out,
- upright and stable during use,
- leak-resistant, and
- properly labelled to warn of hazardous waste inside the container.

- When your sharps disposal container is almost full, you will need to follow your community guidelines for the right way to dispose of your sharps disposal container. There may be state or local laws about how you should throw away used needles and syringes. For more information about safe sharps disposal, and for specific information about sharps disposal in the state that you live in, go to the FDA's website at: http://www.fda.gov/safesharpsdisposal.
- Do not dispose of your used sharps disposal container in your household trash unless your community guidelines permit this. Do not recycle your used sharps disposal container.

Keep Glucagon for Injection and all medicines out of the reach of children.

This Instructions for Use has been approved by the U.S. Food and Drug Administration.

Distributed by:

Sportpharm LLC

379 Van Ness Ave 1401,

Torrance, CA 90501

Relabeled by:

Enovachem PHARMACEUTICALS

Torrance, CA 90501